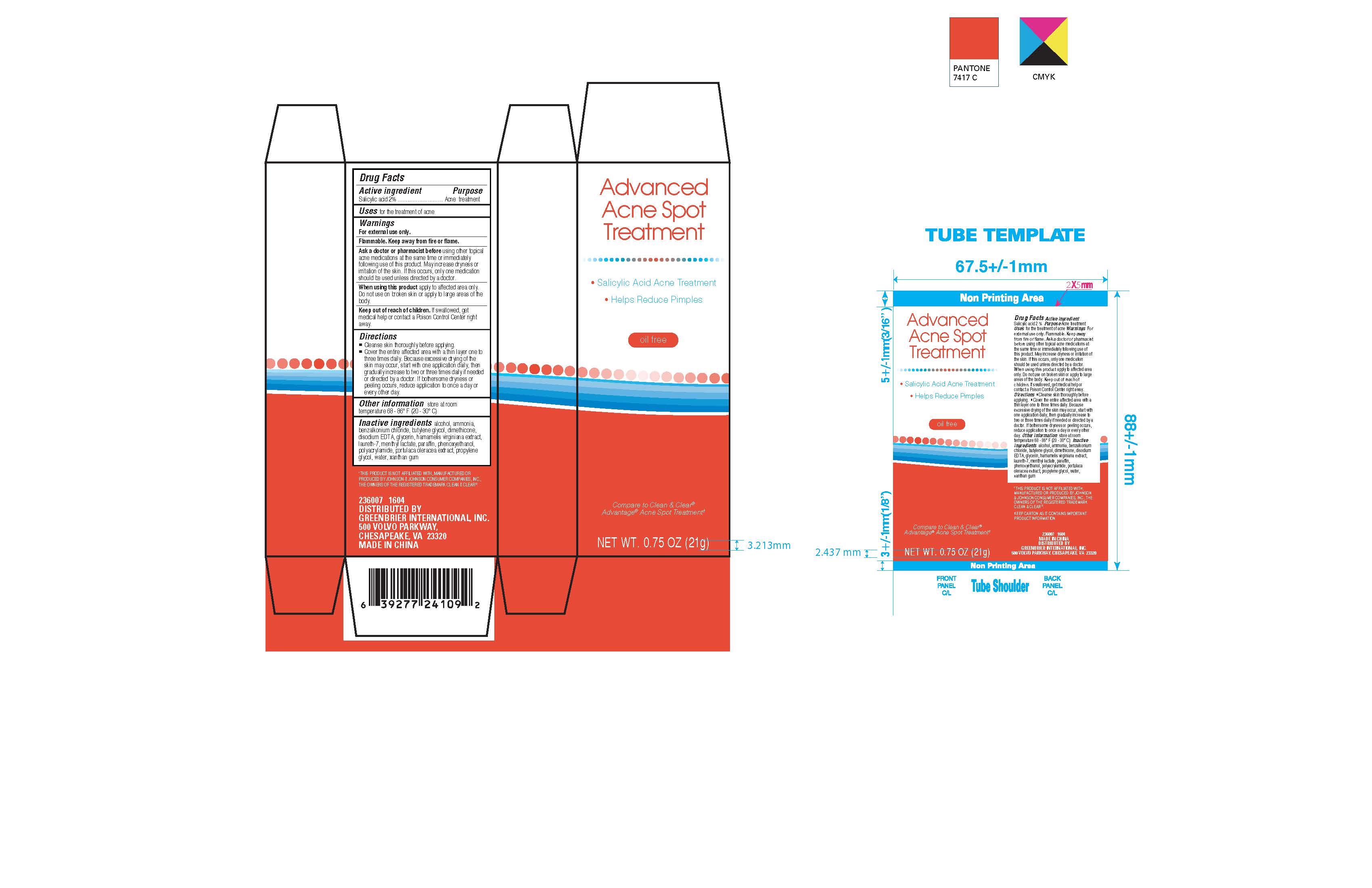 DRUG LABEL: Advanced Acne Spot Treatment
NDC: 58194-030 | Form: GEL
Manufacturer: Shanghai Weierya Daily Chemicals Factory
Category: otc | Type: HUMAN OTC DRUG LABEL
Date: 20160110

ACTIVE INGREDIENTS: SALICYLIC ACID 2 g/100 g
INACTIVE INGREDIENTS: ALCOHOL; AMMONIA; BENZALKONIUM CHLORIDE; BUTYLENE GLYCOL; DIMETHICONE; EDETATE DISODIUM; GLYCERIN; HAMAMELIS VIRGINIANA TOP; LAURETH-7; METHYL LACTATE, (-)- ; PARAFFIN; PHENOXYETHANOL; POLYACRYLAMIDE (1300000 MW); PURSLANE; PROPYLENE GLYCOL; WATER; XANTHAN GUM

Drug Facts

Active ingredient

Salicylic acid 2%

Purpose

Acne treatment

INDICATIONS AND USAGE

Uses for the treatment of acne

Warnings

For external use only.

Flammable. Keep away from fire or flame.

Ask a doctor or pharmacist before using other topical

acne medications at the same time or immediately

following use of this product. May increase dryness or

irritation of the skin. If this occurs, only one medication

should be used unless directed by a doctor.

When using this product apply to affected area only.

Do not use on broken skin or apply to large areas of the

body.

Keep out of reach of children. If swallowed, get

medical help or contact a Poison Control Center right

away.

Directions

-Cleanse skin thoroughly before applying.

-Cover the entire affected area with a thin layer one to

three times daily. Because excessive drying of the skin

may occur, start with one application daily, then

gradually increase to two or three times daily if needed

or directed by a doctor. If bothersome dryness or

peeling occurs, reduce application to once a day or

every other day.

Other information store at room

temperature 68 - 86 F (20 - 30 C)

Inactive ingredients alcohol, ammonia,

benzalkonium chloride, butylene glycol, dimethicone,

disodium EDTA, glycerin, hamamelis virginiana extract,

laureth-7, menthyl lactate, paraffin, phenoxyethanol,

polyacrylamide, portaluca oleracea extract, propylene

glycol, water, xanthan gum